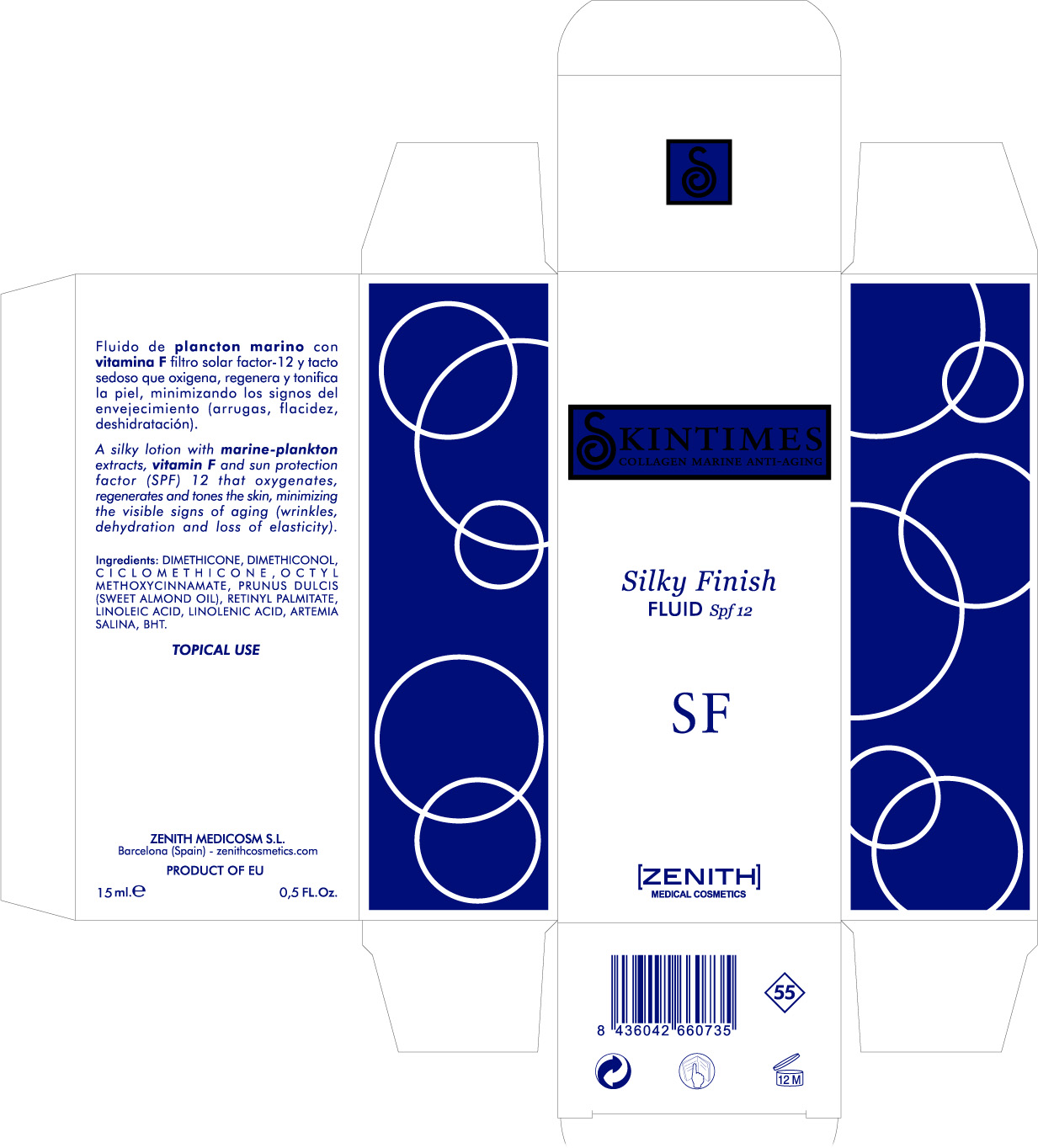 DRUG LABEL: Silky Finish
NDC: 42248-126 | Form: LOTION
Manufacturer: Zenith Medicosm SL
Category: otc | Type: HUMAN OTC DRUG LABEL
Date: 20120218

ACTIVE INGREDIENTS: OCTINOXATE 1.125 mL/15 mL
INACTIVE INGREDIENTS: DIMETHICONE; DIMETHICONOL (41 MPA.S); CYCLOMETHICONE; ALMOND OIL; VITAMIN A PALMITATE; LINOLEIC ACID; LINOLENIC ACID; BUTYLATED HYDROXYTOLUENE

Drug Facts

Active Ingredient

Octinoxate 7.5%

Description

A silky lotion with marine-plankton extracts, vitamin F ans sun protection factor (SPF) 12 that oxygenates, regenerates and tones the skin, minimizing the visible signs of aging (wrinkles, dehydration and lack of elasticity).

15ml. 0.5 FL.oz

Warning

TOPICAL USE